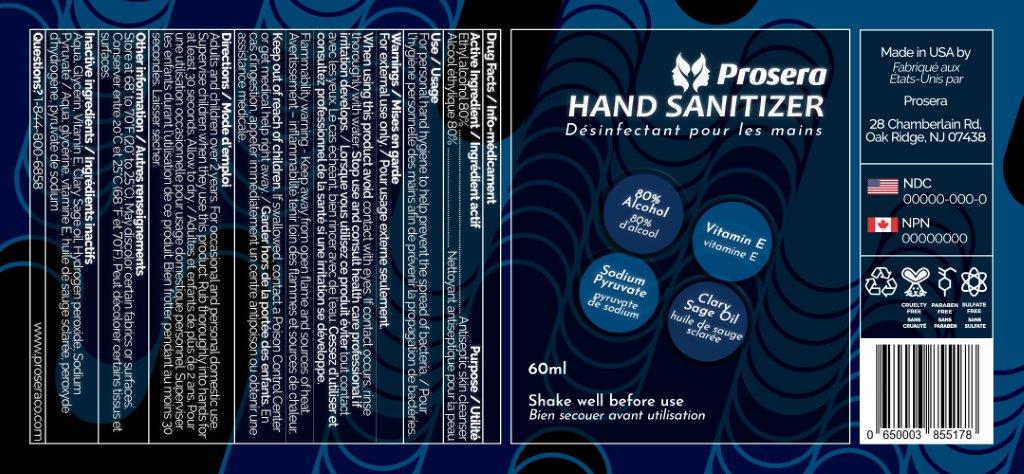 DRUG LABEL: Prosera Hand Sanitizer
NDC: 75306-008 | Form: SPRAY
Manufacturer: D-Time Limited Liability Company
Category: otc | Type: HUMAN OTC DRUG LABEL
Date: 20211102

ACTIVE INGREDIENTS: ALCOHOL 80 mL/100 mL
INACTIVE INGREDIENTS: WATER; GLYCERIN; .ALPHA.-TOCOPHEROL; SAGE OIL; HYDROGEN PEROXIDE; SODIUM PYRUVATE

Active Ingredient

Ethyl alcohol 80%

Purpose

Antiseptic skin cleanser

Uses

For personal hand hygiene to help prevent the spread of bacteria

Warnings

For external use only

When using this product avoid contact with eyes. If contact occurs, rinse thoroughly with water.

Stop use and consult a healthcare professional if irritation develops.

Flammable. Keep away from open flame and sources of heat

Keep out of reach of children.

If swallowed, contact a Poison Control Center or , get medical help right away.

Directions

- Adults and children over 2 years: ∙
- For occasional and personal domestic use ∙
- Supervise children when they use this product ∙
- Rub thoroughly into hands for at least 30 seconds. Allow to dry.

Inactive ingredients

Aqua, Glycerin, Vitamin E, Sage Oil, Hydrogen peroxide, Sodium pyruvate

Other Information

Store at 68° to 70° F (20° to 25° C). May discolor certain fabrics or surfaces.